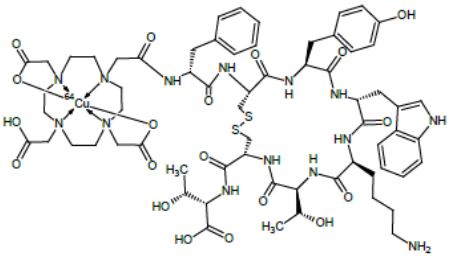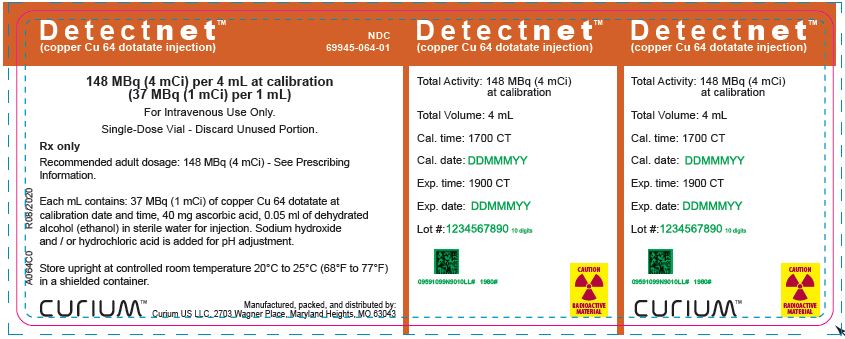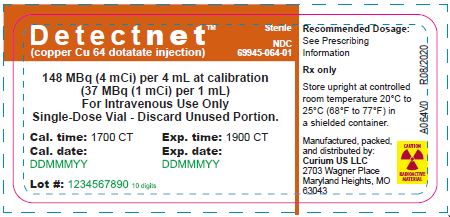 DRUG LABEL: Detectnet
NDC: 69945-064 | Form: INJECTION, SOLUTION
Manufacturer: CURIUM US LLC
Category: prescription | Type: HUMAN PRESCRIPTION DRUG LABEL
Date: 20250131

ACTIVE INGREDIENTS: COPPER OXODOTREOTIDE CU-64 1 mCi/1 mL
INACTIVE INGREDIENTS: ASCORBIC ACID 40 mg/1 mL; ALCOHOL 0.05 mL/1 mL; WATER; SODIUM HYDROXIDE; HYDROCHLORIC ACID

HIGHLIGHTS OF PRESCRIBING INFORMATION

These highlights do not include all the information needed to use DETECTNETTMsafely and effectively. See full prescribing information for DETECTNET.
DETECTNET (copper Cu 64 dotatate injection), for intravenous use
Initial U.S. Approval: 2020

1 INDICATIONS AND USAGE

Detectnet is a radioactive diagnostic agent indicated for use with positron emission tomography (PET) for localization of somatostatin receptor positive neuroendocrine tumors (NETs) in adult patients. (1)

2 DOSAGE AND ADMINISTRATION

- Recommended dose is 148 MBq (4 mCi) administered as an intravenous bolus injection. (2.2)
- Begin acquiring images 45 to 90 minutes after drug administration. (2.4)
- See full prescribing information for additional preparation, administration, imaging and dosimetry information. (2)

3 DOSAGE FORMS AND STRENGTHS

- Injection: 148 MBq (4 mCi) (37 MBq (1 mCi) per 1 mL) of copper Cu 64 dotatate in a single-dose vial.(3)

4 CONTRAINDICATIONS

None (4).

5 WARNINGS AND PRECAUTIONS

- Radiation Risk: Ensure safe handling and preparation procedures to protect patients and health care workers from unintentional radiation exposure (5.1). Advise patients to hydrate before and after administration and to void frequently after administration. (2.3)
- Hypersensitivity Reactions: Most reported reactions were rash and pruritus and reversible either spontaneously or with routine symptomatic management. (5.2)
- Risk for Image Misinterpretation: Uptake of Detectnet can be seen in a variety of tumor types other than NETs, in other pathologic conditions, and as a normal physiologic variant (e.g., uncinate process of the pancreas). (5.3)

6 ADVERSE REACTIONS

Reported adverse reactions include nausea, vomiting, and flushing. (6.1)

To report SUSPECTED ADVERSE REACTIONS, contact CURIUM US LLC at 1-866-789-2211 or FDA at 1-800-FDA-1088 or www.fda.gov/medwatch.

7 DRUG INTERACTIONS

Somatostatin Analogs: Somatostatin analogs competitively bind to the same somatostatin receptors as copper Cu 64 dotatate and may affect imaging. Image patients just prior to dosing with somatostatin analogs. For patients on long-acting somatostatin analogs, a wash-out period of 28 days is recommended prior to imaging. For patients on short-acting somatostatin analogs, a washout period of 2 days is recommended prior to imaging. (2.3, 7.1)

8 USE IN SPECIFIC POPULATIONS

Lactation: Advise patients to interrupt breastfeeding for 12 hours after Detectnet administration. (8.2)

FULL PRESCRIBING INFORMATION

1 INDICATIONS AND USAGE

Detectnet is indicated for use with positron emission tomography (PET) for localization of somatostatin receptor positive neuroendocrine tumors (NETs) in adult patients.

2 DOSAGE AND ADMINISTRATION

2.1 Radiation Safety – Drug Handling

Handle Detectnet with appropriate safety measures to minimize radiation exposure [see Warnings and Precautions (5.1)] . Use waterproof gloves, effective radiation shielding and appropriate safety measures when preparing and handling Detectnet.

Radiopharmaceuticals should be used by or under the control of physicians who are qualified by specific training and experience in the safe use and handling of radionuclides, and whose experience and training have been approved by the appropriate governmental agency authorized to license the use of radionuclides.

2.2 Recommended Dosage and Administration Instructions

Recommended Dosage

In adults, the recommended amount of radioactivity to be administered for PET imaging is 148 MBq (4 mCi) administered as an intravenous injection over a period of approximately 1 minute.

Administration

- Use Detectnet within 2 hours after calibration time.
- Use aseptic technique and radiation shielding when withdrawing and administering Detectnet.
- Inspect Detectnet visually for particulate matter and discoloration before administration. Do not use the drug if the solution contains particulate matter or is discolored.
- Calculate the necessary volume to administer based on measured activity, volume, calibration time, and date.
- Use a dose calibrator to measure the patient dose immediately prior to administration of Detectnet.
- After injection of Detectnet, administer an intravenous flush of 0.9% sodium chloride injection, USP.
- Dispose of any unused drug in a safe manner in compliance with applicable regulations.

2.3 Patient Preparation

Somatostatin Analogs

Image patients just prior to dosing with somatostatin analogs.

For patients on long-acting somatostatin analogs, a wash-out period of 28 days is recommended prior to imaging.

For patients on short-acting somatostatin analogs, a washout period of 2 days is recommended prior to imaging [see Drug Interactions (7.1)] .

Patient Hydration

Instruct patients to drink water to ensure adequate hydration prior to administration of Detectnet and to continue to drink and void frequently during the first hours following administration to reduce radiation exposure [see Warnings and Precautions (5.1)] .

Pregnancy Status

Assessment of pregnancy status is recommended in females of reproductive potential before administering Detectnet.

2.4 Image Acquisition

For Detectnet PET imaging, a whole-body acquisition from the skull vertex to mid-thigh is recommended. Image acquisition can begin between 45 to 90 minutes after the intravenous administration of Detectnet. Adapt Detectnet uptake time and scan duration according to the equipment used and the patient and tumor characteristics, to obtain the optimal image quality.

2.5 Image Interpretation

Copper Cu 64 dotatate binds to somatostatin receptors. Based upon the intensity of the signals, PET images obtained using copper Cu 64 dotatate injection indicate the presence and density of somatostatin receptors in tissues. Uptake can also be seen in a variety of non-NET tumors that contain somatostatin receptors or as a normal physiologic variant [see Warnings and Precautions (5.3)] . NET tumors that do not bear somatostatin receptors will not be visualized.

2.6 Radiation Dosimetry

Estimated radiation absorbed doses per injected activity for organs and tissues of adult patients following an intravenous administration of copper Cu 64 dotatate injection are shown in Table 1.

Table 1. Estimated radiation absorbed dose per injected activity in selected organs with copper Cu 64 dotatate injection
Target Organ | Mean [Mean of 5 patients.] absorbed dose (mGy/MBq)
Adrenals | 0.137
Brain | 0.013
Breasts | 0.013
Gallbladder wall | 0.040
Lower large intestine wall | 0.043
Small intestine | 0.066
Stomach wall | 0.019
Upper large intestine wall | 0.022
Heart wall | 0.019
Kidneys | 0.139
Liver | 0.161
Lungs | 0.017
Muscle | 0.019
Ovaries | 0.019
Pancreas | 0.093
Red marrow | 0.027
Osteogenic cells | 0.034
Skin | 0.012
Spleen | 0.115
Testes | 0.014
Thymus | 0.015
Thyroid | 0.014
Urinary bladder wall | 0.037
Uterus | 0.019
Total body | 0.025
Effective dose (mSv/MBq) | 0.032

The effective radiation dose resulting from the administration of 148 MBq (4 mCi) to an adult is about 4.7 mSv. For an administered activity of 148 MBq (4 mCi) the typical radiation dose to the critical organs, which are the liver, the kidneys/adrenals, and the spleen, are about 24 mGy, 21 mGy and 17 mGy, respectively. Because the spleen has one of the highest physiological uptakes, higher uptake and radiation dose to other organs or pathologic tissues may occur in patients with splenectomy.

3 DOSAGE FORMS AND STRENGTHS

Injection; sterile, clear, colorless to yellow solution in a single-dose vial containing 148 MBq (4 mCi) (37 MBq (1 mCi) per 1 mL) of copper Cu 64 dotatate at calibration date and time.

4 CONTRAINDICATIONS

None.

5 WARNINGS AND PRECAUTIONS

5.1 Radiation Risk

Diagnostic radiopharmaceuticals, including Detectnet, contribute to a patient’s overall long-term cumulative radiation exposure. Long-term cumulative radiation exposure is associated with an increased risk of cancer. Ensure safe handling and preparation procedures to protect patients and health care workers from unintentional radiation exposure. Advise patients to hydrate before and after administration and to void frequently after administration [see Dosage and Administration (2.1, 2.3)] .

5.2 Hypersensitivity Reactions

Hypersensitivity reactions following administration of somatostatin receptor imaging agents predominantly consisted of cutaneous reactions such as rash and pruritus. Reactions reversed either spontaneously or with routine symptomatic management. Less frequently hypersensitivity reactions included angioedema or cases with features of anaphylaxis.

5.3 Risk for Image Misinterpretation

The uptake of copper Cu 64 dotatate reflects the level of somatostatin receptor density in NETs, however, uptake can also be seen in a variety of other tumors that also express somatostatin receptors. Increased uptake might also be seen in other non-cancerous pathologic conditions that express somatostatin receptors including thyroid disease or in subacute inflammation, or might occur as a normal physiologic variant (e.g. uncinate process of the pancreas) [see Dosage and Administration (2.5)] .

A negative scan after the administration of Detectnet in patients who do not have a history of NET disease does not rule out disease [see Clinical Studies (14)] .

6 ADVERSE REACTIONS

The following clinically significant adverse reactions are described elsewhere in the labeling:

- Hypersensitivity reactions [see Warnings and Precautions (5.2)]

6.1 Clinical Trials Experience

Because clinical trials are conducted under widely varying conditions, adverse reaction rates observed in the clinical trials of a drug cannot be directly compared to rates in the clinical trials of another drug and may not reflect the rates observed in practice.

In safety and efficacy trials, 71 subjects received a single dose of Detectnet. Of these 71 subjects, 21 were healthy volunteers and the remainder were patients with known or suspected NET.

The following adverse reactions occurred at a rate of < 2%:

- Gastrointestinal Disorders:nausea, vomiting
- Vascular Disorders:flushing

In published clinical experience, 126 patients with known history of NET received a single dose of copper Cu 64 dotatate injection. Four patients were reported to have experienced nausea immediately after injection.

6.2 Postmarketing Experience

The following adverse reactions have been identified during postapproval use of other somatostatin receptor imaging agents. Because these reactions are reported voluntarily from a population of uncertain size, it is not always possible to reliably estimate their frequency or establish a causal relationship to the drug.

Immune System Disorders:Hypersensitivity reactions, predominantly rash, pruritus, less frequently angioedema or features of anaphylaxis

7 DRUG INTERACTIONS

7.1 Somatostatin Analogs

Non-radioactive somatostatin analogs and copper Cu 64 dotatate competitively bind to somatostatin receptors (SSTR2). Image patients just prior to dosing with somatostatin analogs. For patients on long-acting somatostatin analogs, a wash-out period of 28 days is recommended prior to imaging. For patients on short-acting somatostatin analogs, a washout period of 2 days is recommended prior to imaging [see Dosage and Administration (2.3)].

8 USE IN SPECIFIC POPULATIONS

8.1 Pregnancy

Risk Summary

All radiopharmaceuticals, including Detectnet have the potential to cause fetal harm depending on the fetal stage of development and the magnitude of the radiation dose. Advise a pregnant woman of the potential risks of fetal exposure to radiation from administration of Detectnet.

There are no data on Detectnet use in pregnant women to evaluate for a drug-associated risk of major birth defects, miscarriage, or adverse maternal or fetal outcomes. No animal reproduction studies have been conducted with copper Cu 64 dotatate injection.

The estimated background risk of major birth defects and miscarriage for the indicated population is unknown. All pregnancies have a background risk of birth defects, loss, or other adverse outcomes. In the U.S. general population, the estimated background risk of major birth defects and miscarriage in clinically recognized pregnancies is 2% to 4% and 15% to 20%, respectively.

8.2 Lactation

Risk Summary

There are no data on the presence of copper Cu 64 dotatate in human milk, the effect on the breastfed infant, or the effect on milk production. Lactation studies have not been conducted in animals.

Advise a lactating woman to interrupt breastfeeding for 12 hours after Detectnet administration in order to minimize radiation exposure to a breastfed infant.

8.4 Pediatric Use

The safety and effectiveness of Detectnet have not been established in pediatric patients.

8.5 Geriatric Use

Clinical studies of Detectnet did not include sufficient numbers of subjects aged 65 and over to determine whether they respond differently from younger subjects. Other reported clinical experience has not identified differences in responses between the elderly and younger patients. In general, dose selection for an elderly patient should be cautious, usually starting at the low end of the dosing range, reflecting the greater frequency of decreased hepatic, renal, or cardiac function, and of concomitant disease or other drug therapy.

10 OVERDOSAGE

In the event of a radiation overdose, the absorbed dose to the patient should be reduced where possible by increasing the elimination of the radionuclide from the body by reinforced hydration and frequent bladder voiding. A diuretic might also be considered. If possible, estimation of the radioactive dose given to the patient should be performed.

11 DESCRIPTION

11.1 Chemical Characteristics

Detectnet contains copper Cu 64 dotatate, which is a radioactive diagnostic drug for use with PET imaging. Chemically, copper Cu 64 dotatate is described as copper (Cu 64)-N-[(4,7,10-Tricarboxymethyl-1,4,7,10- tetraazacyclododec-1-yl) acetyl]-Dphenylalanyl-L-cysteinyl-L-tyrosyl-D-tryptophanyl-L-lysyl-L- threoninyl-L-cysteinyl-L-threonine-cyclic (2-7) disulfide. The molecular weight is 1497.2 Daltons and the following is the structural formula:

Detectnet is a sterile, clear, colorless to yellow solution for intravenous use. Each 10 mL single-dose vial contains 148 MBq (4 mCi) of copper Cu 64 dotatate at calibration date and time in 4 mL solution volume. Additionally, each mL of the solution contains 40 mg ascorbic acid, 0.05 ml of dehydrated alcohol, USP (ethanol) in sterile water for injection, USP. The pH is adjusted with sodium hydroxide, hydrochloric acid and is between 5.5 to 7.5.

11.2 Physical Characteristics

Table 2 and Table 3 display the principal radiation emission data and physical decay of copper Cu 64.

Copper Cu 64 decays with a half-life t1/2=12.7 hours:

- 17.6% by positron emission to Ni 64 followed by emission of two 511 keV annihilation photons,
- 38.5% by beta decay to Zn 64,
- 43.8% by electron capture to Ni 64, and
- 0.475% by gamma radiation/internal conversion.

Table 2. Principal radiation emission data (>1%) of copper Cu 64
Radiation/Emission | % Disintegration | Mean Energy (keV)
Positron (β^+) | 17.6 | 278
Beta (β^-) | 38.5 | 190.7
Gamma (γ) | 35.7 0.48 | 511 1346

Table 3. Physical decay chart of copper Cu 64
Hours | Fraction Remaining | Hours | Fraction Remaining
0 | 1.00 | 18 | 0.374
1 | 0.947 | 24 (1 day) | 0.270
3 | 0.849 | 36 (1.5 days) | 0.140
6 | 0.721 | 48 (2 days) | 0.073
9 | 0.612 | 72 (3 days) | 0.020
12 | 0.520 | 96 (4 days) | 0.005

11.3 External Radiation

Gamma constant: 3.6 X 10^-5mSv/hr per MBq at 1 meter (0.133 mrem/hr per mCi at 1 meter)
Table 4 displays the radiation attenuation by lead shielding of copper Cu 64.

Table 4. Radiation attenuation of copper Cu 64 by lead shielding
Shield Thickness cm of Lead (Pb) | Coefficient of Attenuation
0.51 | 0.5
1.60 | 0.1
3.45 | 0.01
6.83 | 0.001

12 CLINICAL PHARMACOLOGY

12.1 Mechanism of Action

Copper Cu 64 dotatate binds to somatostatin receptors with highest affinity for subtype 2 receptors (SSTR2). It binds to cells that express somatostatin receptors including malignant neuroendocrine cells, which overexpress SSTR2 receptors. Copper Cu 64 is a positron (β^+) emitting radionuclide with an emission yield that allows positron emission tomography (PET) imaging.

12.2 Pharmacodynamics

The relationship between copper Cu 64 dotatate plasma concentrations and successful imaging was not explored in clinical trials.

12.3 Pharmacokinetics

Distribution

After 1 to 3 hours of a single dose administration of copper Cu 64 dotatate injection, the maximum radioactivity is observed in adrenal glands, kidney, pituitary glands, spleen, and liver.

Elimination

Metabolism

The metabolism of copper Cu 64 dotatate is unknown.

Excretion

Following a single intravenous dose (4.15 ± 0.13 mCi) of Detectnet (n = 6), between 16% to 40% radioactivity of the injected dose was recovered in urine over a 6-hour collection time.

Specific Populations

The effect of hepatic impairment or renal impairment on copper Cu 64 dotatate pharmacokinetics has not been studied.

13 NONCLINICAL TOXICOLOGY

13.1 Carcinogenesis, Mutagenesis, Impairment of Fertility

Carcinogenicity and mutagenicity studies have not been conducted with copper Cu 64 dotatate injection; however, radiation is a carcinogen and mutagen.

No animal studies were conducted to determine the effects of copper Cu 64 dotatate on fertility or embryology.

14 CLINICAL STUDIES

The efficacy of Detectnet was established in two single-center, open-label studies. Study 1 prospectively evaluated a total of 63 subjects, including 42 patients with known or suspected NET based on histology, conventional imaging, or clinical evaluations and 21 healthy volunteers. Of the 42 patients, 37 (88%) had a history of NETs at the time of Detectnet imaging. Among the total study population of 63 subjects, 28 (44%) were men and 35 (56%) were women with most subjects being white (86%). The mean age of the subjects was 54 years (range 25 to 82 years).

Detectnet images from each subject were interpreted as either positive or negative for NET by three independent readers who were blinded to clinical information and other imaging results. PET imaging results were compared to a composite reference standard consisting of a single oncologist’s blinded assessment of subject diagnosis based on available histopathology results, reports of conventional imaging (MRI, contrast CT, bone scintigraphy, F 18 fludeoxyglucose PET/CT, F 18 sodium fluoride PET/CT, In 111 pentetreotide SPECT/CT, Ga 68 dotatate PET/CT) performed within 8 weeks prior to Detectnet imaging, and clinical and laboratory data including chromogranin A and serotonin levels. The proportion of subjects positive for disease per composite reference who were identified as positive by Detectnet imaging was used to quantify positive percent agreement. The proportion of subjects without disease per composite reference who were identified as negative by Detectnet imaging was used to quantify negative percent agreement. Table 5 shows the performance of Detectnet in the detection of NET for Study 1.

Table 5: Performance of Detectnet in the detection of NET by reader in Study 1
 | NET status as identified by reader | Reference
 | NET status as identified by reader | Positive | Negative
Reader 1; (n=62)* | Positive | 30 | 1
Reader 1; (n=62)* | Negative | 3 | 28
Reader 1; (n=62)*
Reader 1; (n=62)* | Percent Reader Agreement; (95% CI)** | 91 (75, 98) | 97 (80, 99)
Reader 2; (n=63) | Positive | 30 | 6
Reader 2; (n=63) | Negative | 3 | 24
Reader 2; (n=63)
Reader 2; (n=63) | Percent Reader Agreement; (95% CI)** | 91 (75, 98) | 80 (61, 92)
Reader 3; (n=63) | Positive | 30 | 3
Reader 3; (n=63) | Negative | 3 | 27
Reader 3; (n=63)
Reader 3; (n=63) | Percent Reader Agreement; (95% CI)** | 91 (75, 98) | 90 (72, 97)
n: number of patients, CI: confidence interval, *Reader 1 interpreted one of the 63 PET scans as “not evaluable”, **Wilson score interval with continuity correction

Study 2 showed similar performance through retrospective analysis of published data collected in 112 patients (63 males, 49 females; mean age 62 years, range 30 to 84 years) with a known history of NET.

16 HOW SUPPLIED/STORAGE AND HANDLING

How Supplied

Detectnet (NDC 69945-064-01) is supplied as a sterile, clear, colorless to yellow solution in a 10 mL single-dose vial containing 148 MBq (4 mCi) (37 MBq (1 mCi) per mL) of copper Cu 64 dotatate at calibration date and time.

The sealed vial is contained in a shielded (lead) container for radiation protection. The product is shipped in a Type A package.

Discard unused portion from the single-patient use vial.

Storage and Handling

Store Detectnet in an upright position within the lead shielding to protect handlers from exposure to radiation.

Store Detectnet at controlled room temperature 20°C to 25°C (68°F to 77°F). Do not use and discard Detectnet 2 hours after the calibration date and time.

This radiopharmaceutical is for distribution and use by persons under license by the U.S. Nuclear Regulatory Commission or the relevant regulatory authority of an Agreement State. Store and dispose of Detectnet in compliance with the appropriate regulations of the government agency authorized to license the use of this radionuclide.

17 PATIENT COUNSELING INFORMATION

Radiation Risk

Advise patients to drink water to ensure adequate hydration prior to their PET study and recommend they drink and urinate as often as possible during the first hours following the administration of Detectnet, in order to reduce radiation exposure [see Dosage and Administration (2.3) and Warnings and Precautions (5.1)] .

Pregnancy

Advise a pregnant woman of the potential risks of fetal exposure to radiation doses with Detectnet [see Use in Specific Populations (8.1)] .

Lactation

Advise a lactating woman to interrupt breastfeeding for 12 hours after Detectnet administration in order to minimize radiation exposure to a breastfed infant [see Use in Specific Populations (8.2)] .

Manufactured, Packed and Distributed by:
Curium US LLC
2703 Wagner Place
Maryland Heights, MO 63043

© 2025 Curium US LLC
DetectnetTM, CuriumTM, and the Curium logo are trademarks of a Curium company.

Principal Display Panel - Vial

Detect netTM Sterile
(copper Cu 64 dotatate injection) NDC 69945-064-01

148 MBq (4 mCi) per 4 mL at calibration
(37 MBq (1 mCi) per 1 mL)
For Intravenous Use Only
Single-Dose Vial - Discard Unused Portion.

Cal. time:1700 CT Exp. time:1900 CT

Cal. date: Exp. date:

Lot #:

Principal Display Panel - Can

Detect netTM
(copper Cu 64 dotatate injection) NDC 69945-064-01

148 MBq (4 mCi) per 4 mL at calibration
(37 MBq (1 mCi) per 1 mL)

For Intravenous Use Only.
Single-Dose Vial - Discard Unused Portion.

Rx only

Recommended adult dosage: 148 MBq (4 mCi) - See Prescribing
Information.
Each mL contains: 37 MBq (1 mCi) of copper Cu 64 dotatate at
calibration date and time, 40 mg ascorbic acid, 0.05 ml of dehydrated
alcohol (ethanol) in sterile water for injection. Sodium hydroxide
and / or hydrochloric acid is added for pH adjustment.

Store upright at controlled room temperature 20°C to 25°C (68°F to 77°F)
in a shielded container.

CURIUMTM

Manufactured, packed, and distributed by:
Curium US LLC. 2703 Wagner Place, Maryland Heights, MO 63043